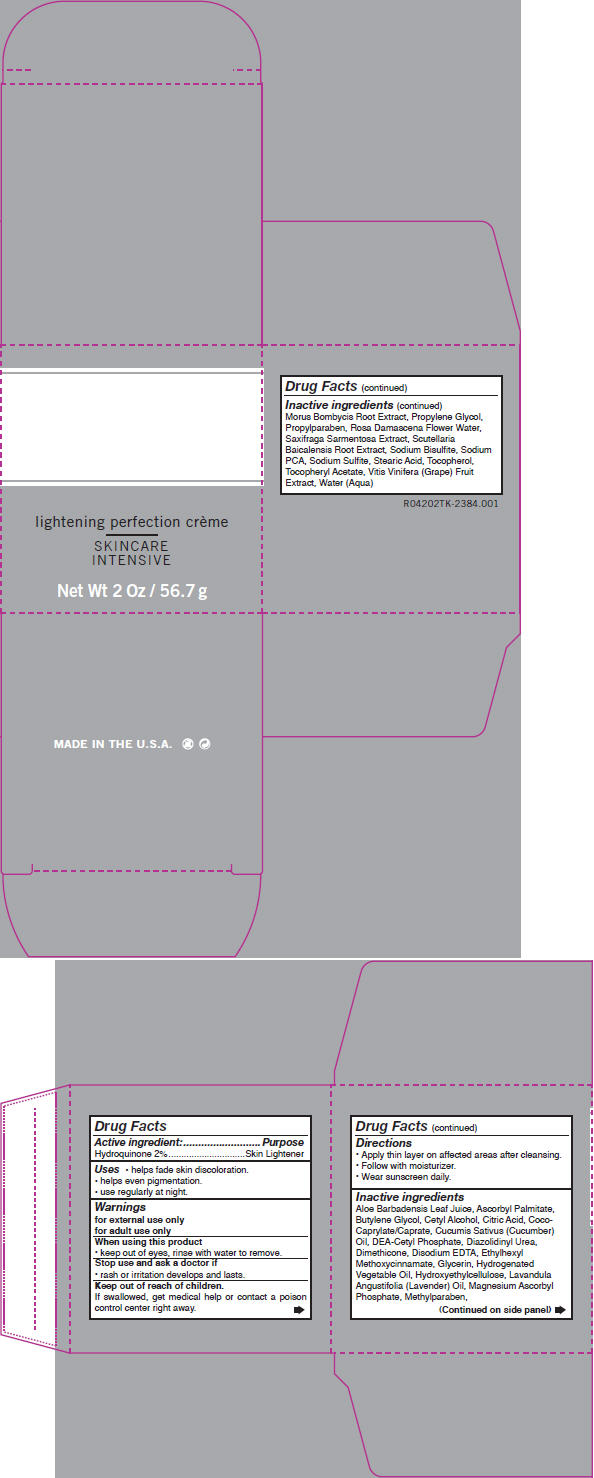 DRUG LABEL: Advanced Lightning
NDC: 24623-042 | Form: CREAM
Manufacturer: CBI Laboratories, Inc
Category: otc | Type: HUMAN OTC DRUG LABEL
Date: 20110105

ACTIVE INGREDIENTS: OCTINOXATE 0.02 g/1 g; HYDROQUINONE 0.02 g/1 g
INACTIVE INGREDIENTS: GLYCERIN; ALOE VERA LEAF; CETYL ALCOHOL; DIETHANOLAMINE CETYL PHOSPHATE; WATER; DIMETHICONE 350; SODIUM SULFITE; DIAZOLIDINYL UREA; ALPHA-TOCOPHEROL ACETATE; STEARIC ACID; ASCORBYL PALMITATE; SODIUM METABISULFITE; CITRIC ACID MONOHYDRATE; EDETATE DISODIUM; SODIUM PYRROLIDONE CARBOXYLATE; CUCUMBER; MAGNESIUM ASCORBYL PHOSPHATE; ROSA DAMASCENA FLOWER OIL

lightening perfection crème
SKINCARE
INTENSIVE

Drug Facts

Active ingredient

Hydroquinone 2%

Purpose

Skin Lightener

Uses

- helps fade skin discoloration.
- helps even pigmentation.
- use regularly at night.

Warnings

for external use only

for adult use only

When using this product

- keep out of eyes, rinse with water to remove.

Stop use and ask a doctor if

- rash or irritation develops and lasts.

Keep out of reach of children.

If swallowed, get medical help or contact a poison control center right away.

Directions

- Apply thin layer on affected areas after cleansing.
- Follow with moisturizer.
- Wear sunscreen daily.

Inactive ingredients

Aloe Barbadensis Leaf Juice, Ascorbyl Palmitate, Butylene Glycol, Cetyl Alcohol, Citric Acid, Coco-Caprylate/Caprate, Cucumis Sativus (Cucumber) Oil, DEA-Cetyl Phosphate, Diazolidinyl Urea, Dimethicone, Disodium EDTA, Ethylhexyl Methoxycinnamate, Glycerin, Hydrogenated Vegetable Oil, Hydroxyethylcellulose, Lavandula Angustifolia (Lavender) Oil, Magnesium Ascorbyl Phosphate, Methylparaben, Morus Bombycis Root Extract, Propylene Glycol, Propylparaben, Rosa Damascena Flower Water, Saxifraga Sarmentosa Extract, Scutellaria Baicalensis Root Extract, Sodium Bisulfite, Sodium PCA, Sodium Sulfite, Stearic Acid, Tocopherol, Tocopheryl Acetate, Vitis Vinifera (Grape) Fruit Extract, Water (Aqua)

PRINCIPAL DISPLAY PANEL - 56.7 g Carton

lightening perfection crème

SKINCARE
INTENSIVE

Net Wt 2 Oz / 56.7 g